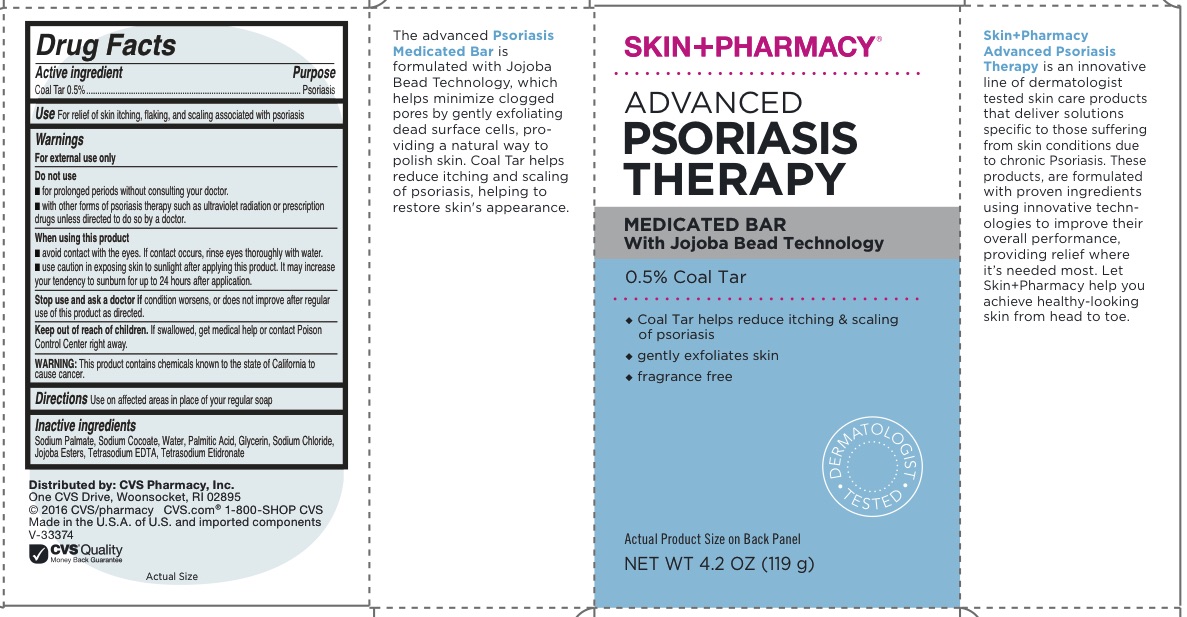 DRUG LABEL: ADVANCED PSORIASIS THERAPY
NDC: 69842-344 | Form: SOAP
Manufacturer: CVS Pharmacy, Inc.
Category: otc | Type: HUMAN OTC DRUG LABEL
Date: 20160610

ACTIVE INGREDIENTS: COAL TAR 5 g/1000 g
INACTIVE INGREDIENTS: WATER; SODIUM PALMATE; SODIUM COCOATE; PALMITIC ACID; GLYCERIN; SODIUM CHLORIDE; ETIDRONATE TETRASODIUM; EDETATE SODIUM; HYDROGENATED JOJOBA OIL

ADVANCED PSORIASIS THERAPY

Active Ingredient

Coal Tar 0.5%

Purpose

Psoriasis Relief

Use

For relief of skin itching, flaking, and scaling associated with psoriasis

Warnings

For external use only

- Keep out of the reach of children.
- If swallowed, get medical help or contact a Poison Control Center immediately.

Directions

- Use on affected areas in place of your regular soap

When using this product

■ avoid contact with the eyes. If contact occurs, rinse eyes thoroughly with water.
■ use caution in exposing skin to sunlight after applying this product. It may increase your tendency to sunburn for up to 24 hours after application.

Stop use and ask a doctor if ■ condition worsens, or does not improve after regular use of this product as directed.

Do not use

■ for prolonged periods without consulting your doctor.
■ with other forms of psoriasis therapy such as ultraviolet radiation or prescription drugs unless directed to do so by a doctor.

WARNING

This product contains chemicals known to the state of California to cause cancer.

INACTIVE INGREDIENT

Sodium Palmate, Sodium Cocoate, Water, Palmitic Acid, Glycerin, Sodium Chloride, Jojoba Esters, Tetrasodium EDTA, Tetrasodium Etidronate

Questions?

www.CVS.com

1-800-SHOP CVS